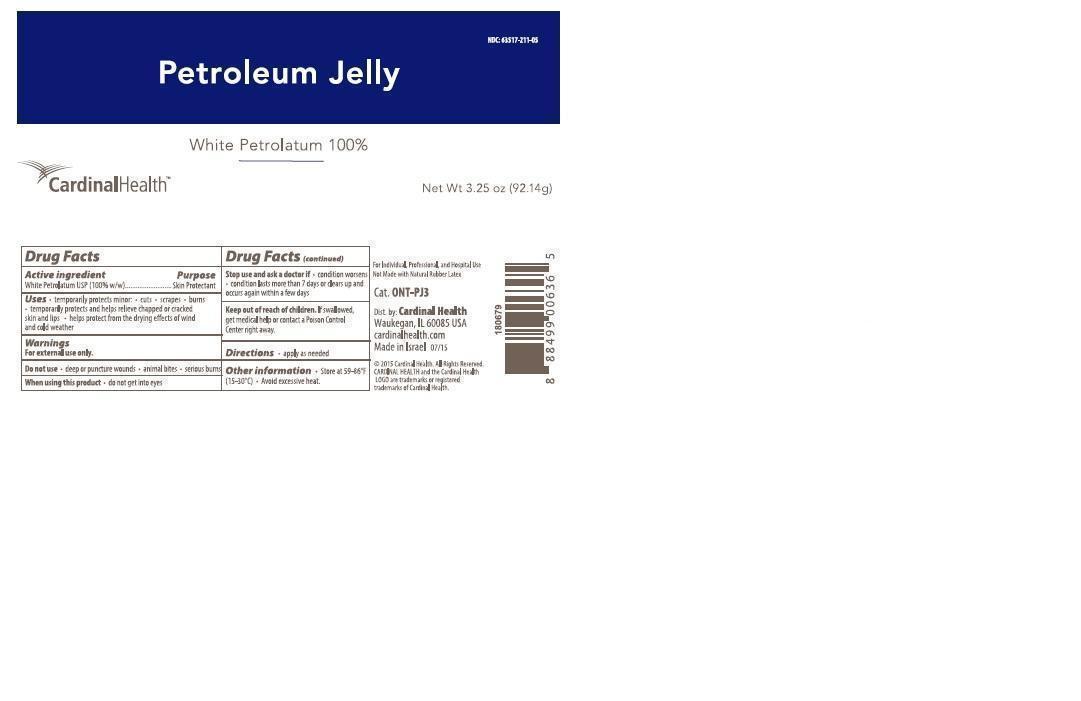 DRUG LABEL: PETROLEUM
NDC: 63517-211 | Form: JELLY
Manufacturer: Cardinal Health
Category: otc | Type: HUMAN OTC DRUG LABEL
Date: 20221212

ACTIVE INGREDIENTS: PETROLATUM 1 g/1 g

Petrolatum Jelly

Active Ingredient

White Petrolatum (USP, 100% w/w)

Purpose

Skin Protectant

Uses:

- temporarily protects minor * cuts * scrapes * burns
- temporarily protects and helps relieve chapped and cracked skin or lips
- helps protect from the drying effects of wind and cold weather

Warnings:

For external use only.

Do not use

- deep or puncture wounds
- animal bites
- serious burns

When using this product

- do not get into eyes

Stop use and ask a doctor if

- condition worsens
- condition lasts more than 7 days or clears up and occurs again within a few days

Keep out of reach of children.

If swallowed, get medical help or contact a Poison Control Center right away.

Directions:

- apply as needed.

Inactive Ingredients

None

Other information:

- Store at 59 Deg F - 86 Deg F (15 - 30 Deg C)
- Avoid excessive heat.

Principal Display Panel

Petroleum Jelly

White Petrolatum 100%

Cardinal Health

NDC 63517-211-05

Net Wt 3.25 oz (92.14g)